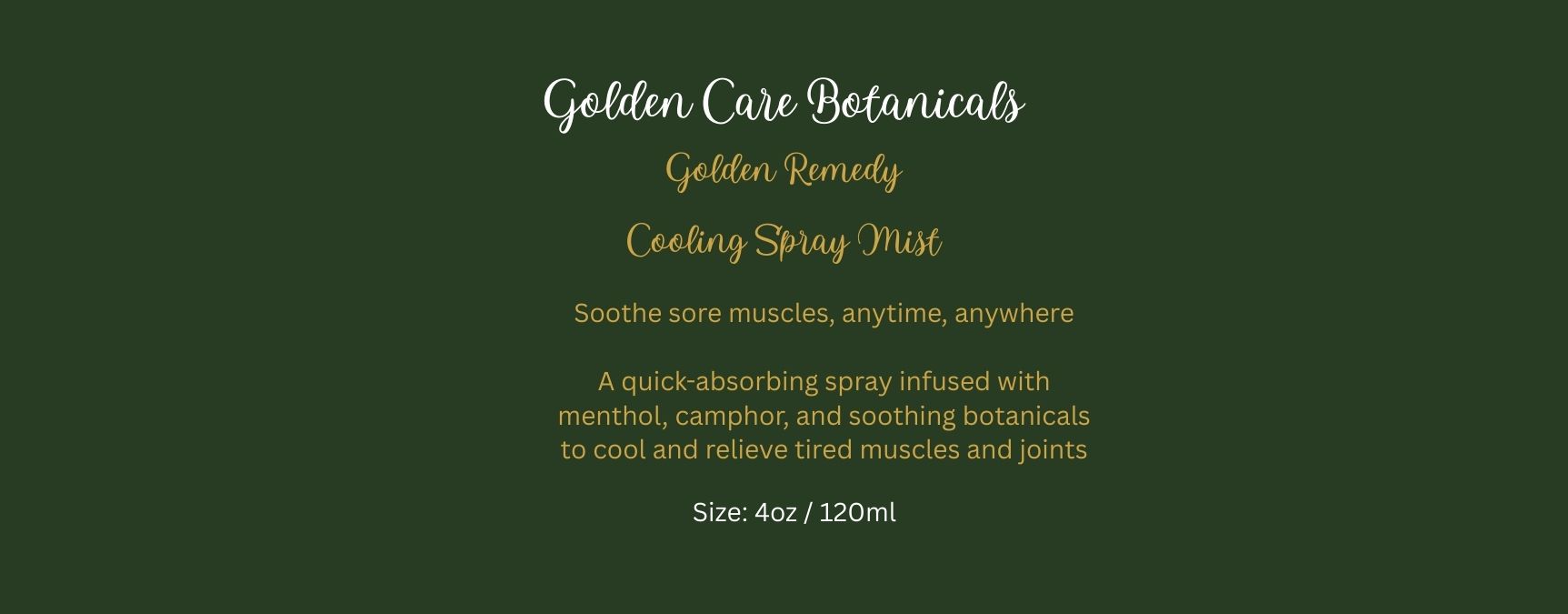 DRUG LABEL: Golden Remedy Cooling Mist
NDC: 87037-003 | Form: SPRAY
Manufacturer: GOLDEN CARE BOTANICALS LLC
Category: otc | Type: HUMAN OTC DRUG LABEL
Date: 20251006

ACTIVE INGREDIENTS: MENTHOL 2 g/2 g; CAMPHOR (NATURAL) 2 g/2 g
INACTIVE INGREDIENTS: GINGER OIL; AVOCADO OIL; HELICHRYSUM GYMNOCEPHALUM WHOLE; FRANKINCENSE; .ALPHA.-TOCOPHEROL ACETATE, D-; PHENOXYETHANOL; CAPRYLYL GLYCOL; WITCH HAZEL; ALOE VERA LEAF JUICE

PURPOSE

Topical analgesic for temporary relief of minor aches and pain of muscles and joints associated with aches, arthritis, or stiffness

Do not use on open wounds, broken skin, or with a heating pad

Stop use and ask a doctor if: condition worsens, or symptoms persist for more than 7 days.

WARNINGS

For external use only

INACTIVE INGREDIENT

Inactive ingredients: avocado oil, helichrysum, frankincense, ginger oil, vitamin e, phenoxyethanol and caprylyl glycol, aloe vera juice, and witch hazel

Directions:
Adults and children 12 years and over: Apply to the affected area not more than 3 to 4 times daily.

Route of Administration:Topical (external) use only

INDICATIONS AND USAGE

Route of Administration:Topical

KEEP OUT OF REACH OF CHILDREN

If swallowed, seek immediate medical attention or contact Poison Control